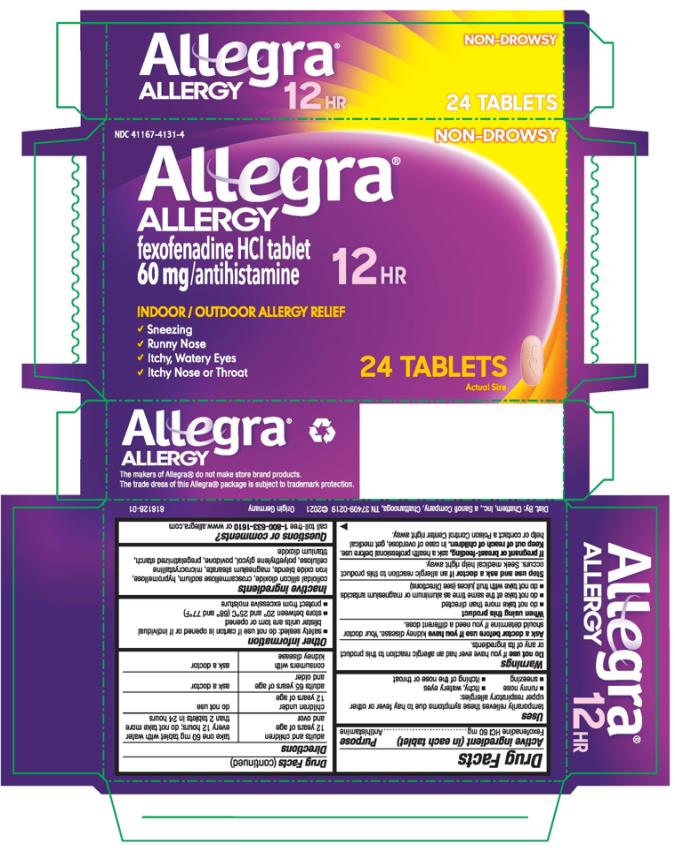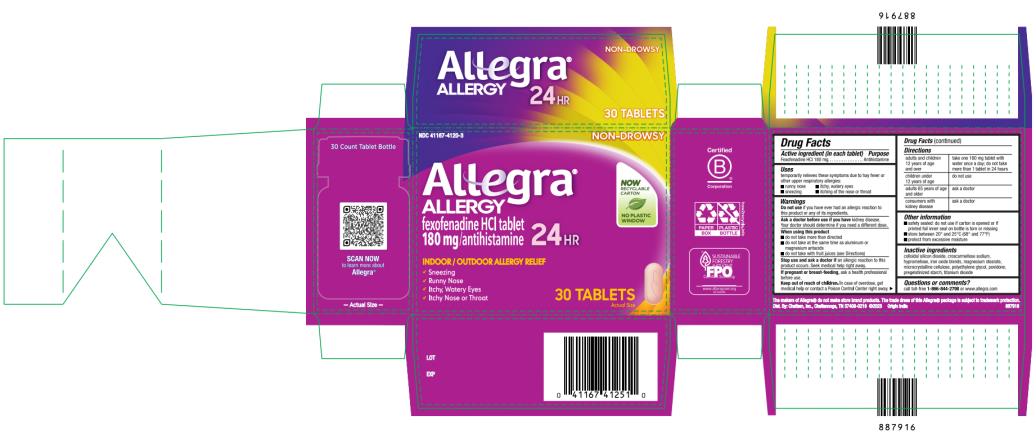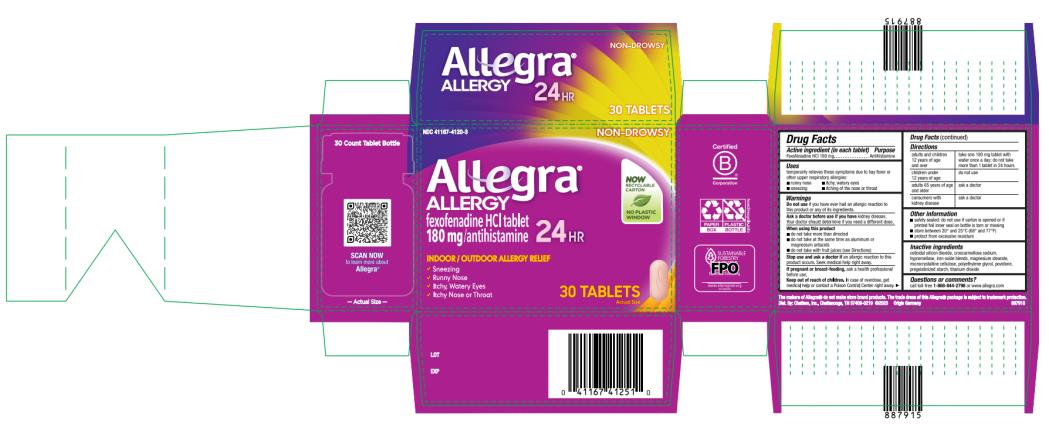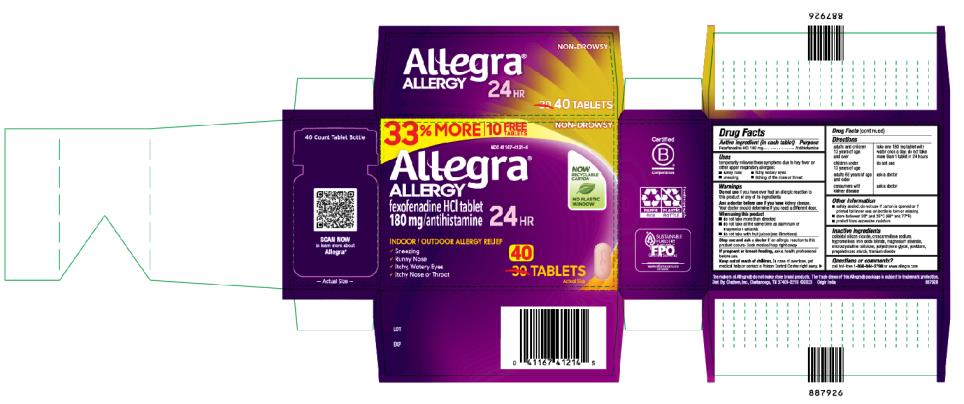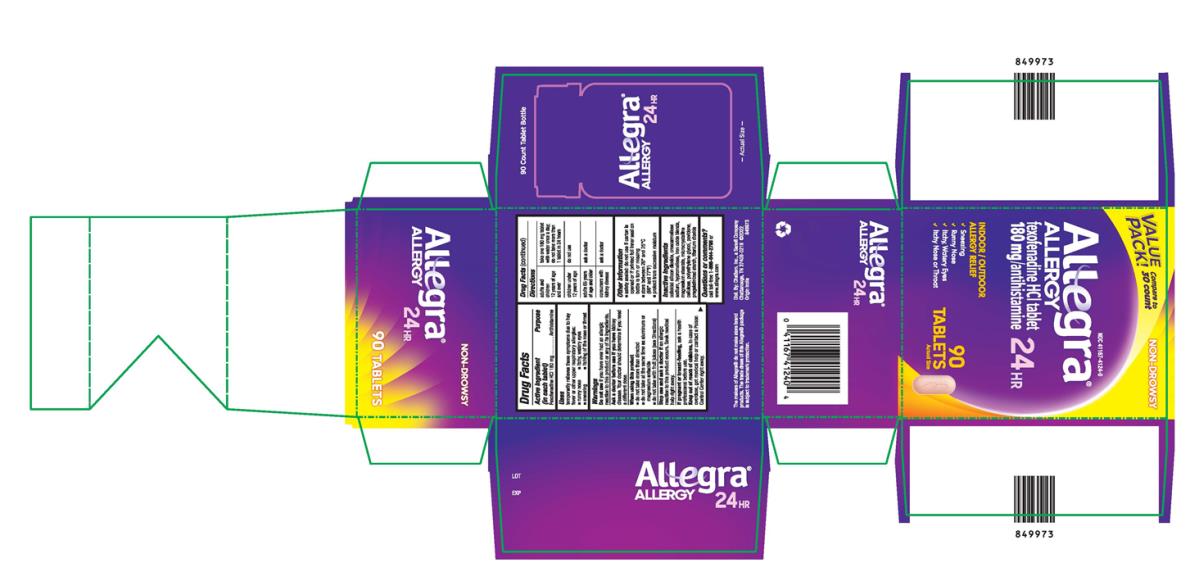 DRUG LABEL: Allegra Allergy
NDC: 41167-4131 | Form: TABLET, FILM COATED
Manufacturer: Chattem, Inc.
Category: otc | Type: HUMAN OTC DRUG LABEL
Date: 20241101

ACTIVE INGREDIENTS: FEXOFENADINE HYDROCHLORIDE 60 mg/1 1
INACTIVE INGREDIENTS: SILICON DIOXIDE; CROSCARMELLOSE SODIUM; HYPROMELLOSES; MAGNESIUM STEARATE; CELLULOSE, MICROCRYSTALLINE; POLYETHYLENE GLYCOL, UNSPECIFIED; POVIDONE; TITANIUM DIOXIDE; STARCH, CORN; BROWN IRON OXIDE

Allegra Allergy

Allegra Allergy

Allegra Allergy® - 12/24 HOUR

Drug Facts

Active ingredient

(in each tablet)
12 Hour Tablet: Fexofenadine HCl 60 mg

24 Hour Tablet: Fexofenadine HCl 180 mg

Purpose

Antihistamine

Uses

temporarily relieves these symptoms due to hay fever or other upper respiratory allergies:

- runny nose
- sneezing
- itchy, water eyes
- itching of the nose or throat

Warnings

Do not use

if you have ever had an allergic reaction to this product or any of its ingredients

Ask a doctor before use if you have

kidney disease. Your doctor should determine if you need a different dose.

When using this product

- do not take more than directed
- do not take at the same time as aluminum or magnesium antacids
- do not take with fruit juices (see Directions)

Stop use and ask a doctor if

an allergic reaction to this product occurs. Seek medical help right away.

If pregnant or breast-feeding,

ask a health professional before use.

Keep out of reach of children.

In case of overdose, get medical help or contact a Poison Control Center right away.

Allegra 12 Hour Directions

adults and children 12 years of age and over | take one 60 mg tablet with water every 12 hours; do not take more than 2 tablets in 24 hours
children under 12 years of age | do not use
adults 65 years of age and older | ask a doctor
consumers with kidney disease | ask a doctor

Allegra 24 Hour Directions

adults and children 12 years of age and over | take one 180 mg tablet with water once a day; do not take more than 1 tablet in 24 hours
children under 12 years of age | do not use
adults 65 years of age and older | ask a doctor
consumers with kidney disease | ask a doctor

Other information

- safety sealed: do not use if carton is opened or if individual blister units are torn or opened or if inner foil seal on bottle is torn or missing
- store between 20° and 25°C (68° and 77°F)
- protect from excessive moisture

Inactive ingredients

colloidal silicon dioxide, croscarmellose sodium, hypromellose, iron oxide blends, magnesium stearate, microcrystalline cellulose, polyethylene glycol, povidone, pregelatinized starch, titanium dioxide

Questions or comments?

call toll-free 1-800-633-1610 or www.allegra.com

PRINCIPAL DISPLAY PANEL

NDC 41167-4131-4
Allegra
ALLERGY
60 mg/ antihistamine
12 HR
24 TABLETS

PRINCIPAL DISPLAY PANEL

NDC 41167-4120-3
Allegra
ALLERGY
180 mg/ antihistamine
24 HR
30 TABLETS

PRINCIPAL DISPLAY PANEL

Allegra
ALLERGY
180 mg/ antihistamine
24 HR
40 TABLETS

PRINCIPAL DISPLAY PANEL

Allegra
ALLERGY
180 mg/ antihistamine
24 HR
90 TABLETS